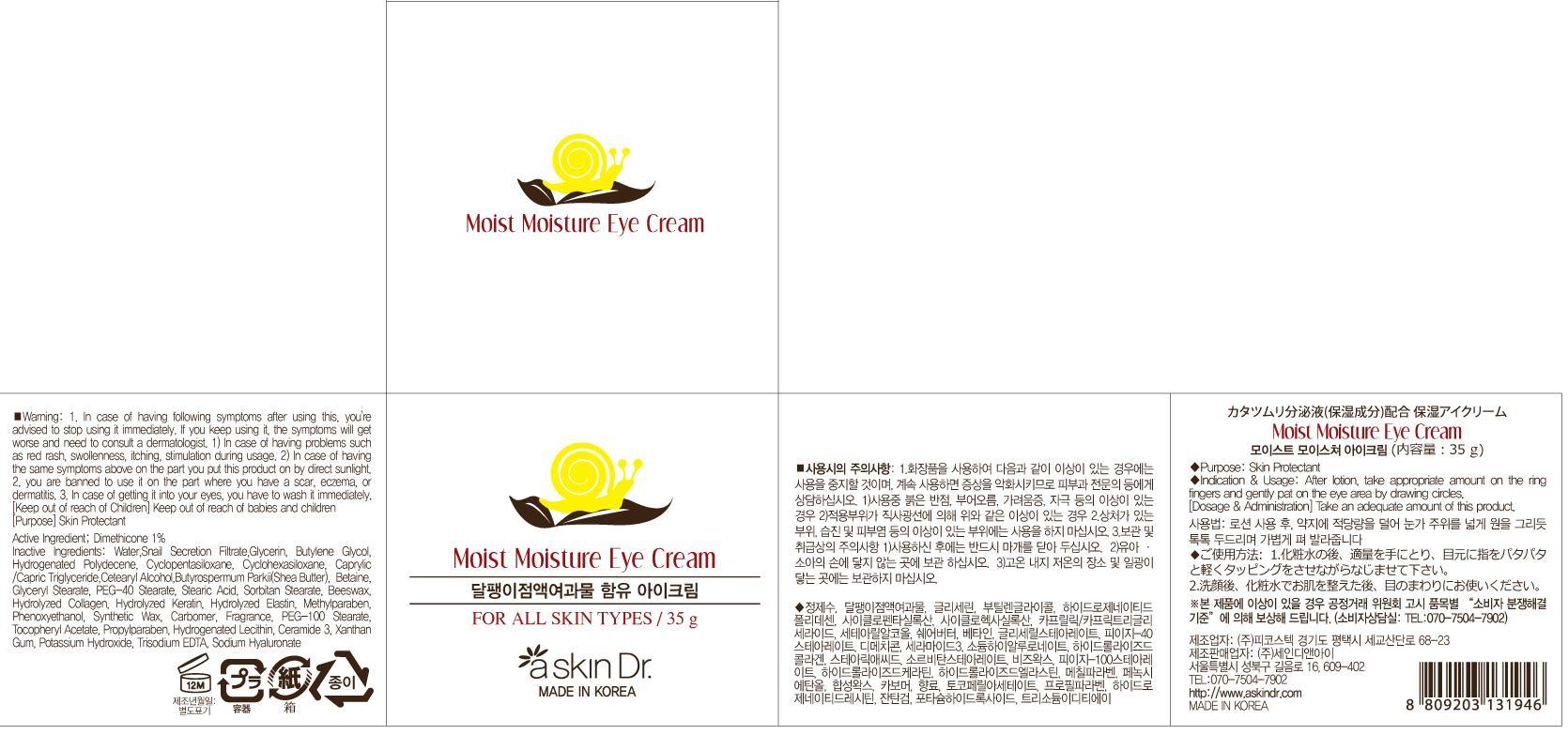 DRUG LABEL: MOIST MOISTURE EYE
NDC: 69072-050 | Form: CREAM
Manufacturer: Seindni Co.,ltd
Category: otc | Type: HUMAN OTC DRUG LABEL
Date: 20181210

ACTIVE INGREDIENTS: Dimethicone 0.35 g/35 g
INACTIVE INGREDIENTS: Water; Glycerin

ACTIVE INGREDIENT

Active Ingredients: Dimethicone 1%

INACTIVE INGREDIENT

Inactive Ingredients:
Water, Snail Secretion Filtrate, Glycerin, Butylene Glycol,Hydrogenated Polydecene,Cyclopentasiloxane, Cyclohexasiloxane,Caprylic/Capric Triglyceride,Cetearyl Alcohol,Butyrospermum Parkii(Shea Butter), Betaine,Glyceryl Stearate,PEG-40 Stearate,Stearic Acid,Sorbitan Stearate,Beeswax,Hydrolyzed Collagen, Hydrolyzed Keratin,Hydrolyzed Elastin,Methylparaben,Phenoxyethanol,Synthetic Wax,Carbomer,Fragrance, PEG -100 Stearate,Tocopheryl Acetate,Propylparaben,Hydrogenated Lecithin,Ceramide 3,Xanthan Gum, Potassium Hydroxide,Trisodium EDTA,Sodium Hyaluronate

PURPOSE

Purpose: Skin Protectant

WARNINGS

Warning:
1. In case of having following symptoms after using this, you're advised to stop using it immediately. If you keep using it, the symptoms will get worse and need to consult a dermatologist. 1) In case of having problems such as red rash, swollenness, itching, stimulation during usage. 2) In case of having the same symptoms above on the part you put this product on by direct sunlight. 2. you are banned to use it on the part where you have a scar, eczema, or dermatitis. 3. In case of getting it into your eyes, you have to wash it immediately.

Keep out of reach of children: Keep out of reach of babies and children

INDICATIONS AND USAGE

Indication and Usage: After lotion, take appropriate amount on the ring fingers and gently pat on the eye area by drawing circles.

Dosage and Administration: Take an adequate amount of this product.